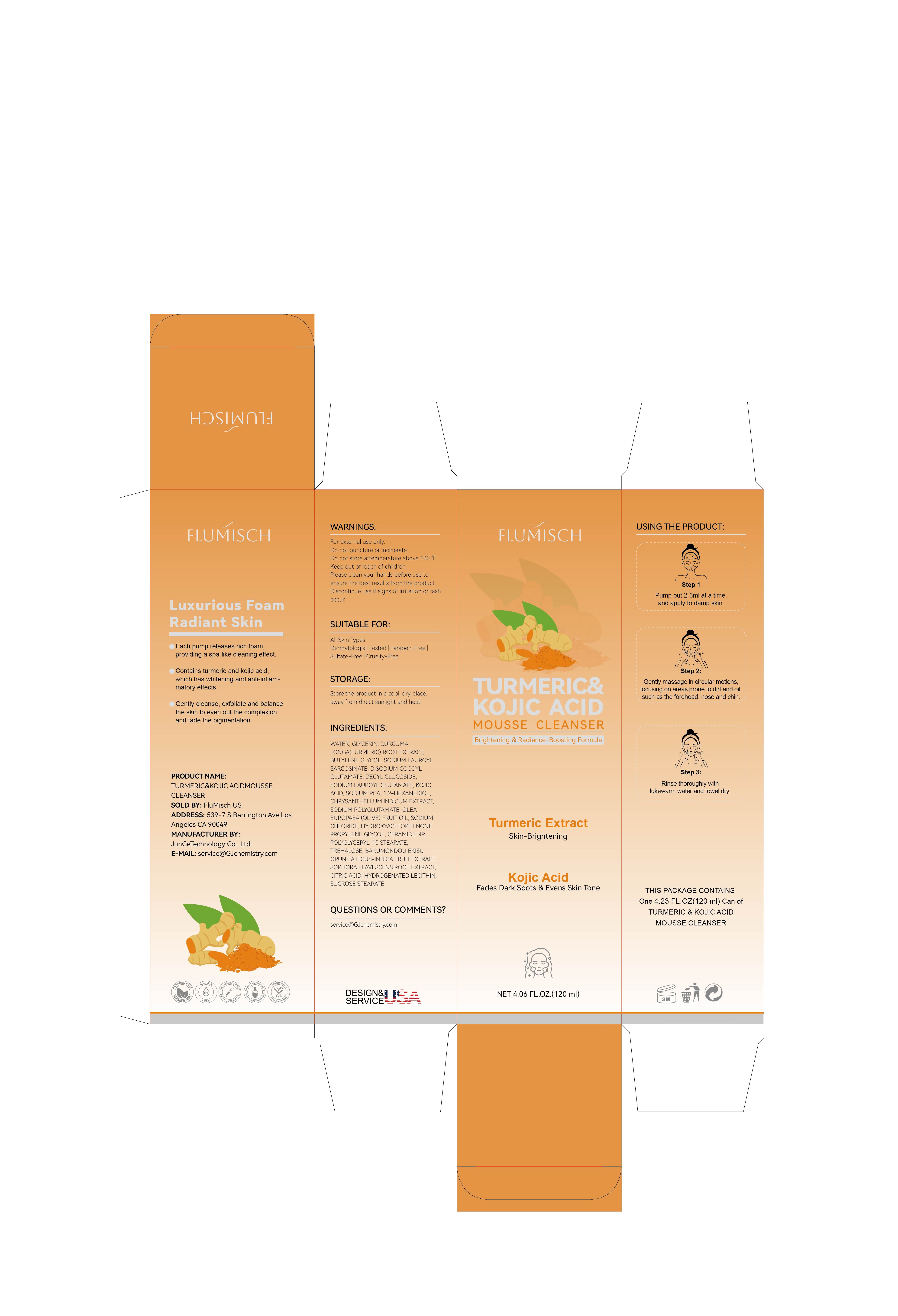 DRUG LABEL: FluMisch Turmeric Kojic Acid Facial Cleanser
NDC: 85212-0003 | Form: AEROSOL, FOAM
Manufacturer: Beijing JUNGE Technology Co., Ltd.
Category: otc | Type: HUMAN OTC DRUG LABEL
Date: 20250212

ACTIVE INGREDIENTS: CURCUMA LONGA (TURMERIC) ROOT POWDER 5 g/100 mL
INACTIVE INGREDIENTS: AQUA 66.45 mL/100 mL; OPHIOPOGON JAPONICUS SEED 0.15 mL/100 mL; CITRIC ACID 0.1 mL/100 mL; SODIUM LAUROYL GLUTAMATE 2 mL/100 mL; HYDROXYACETOPHENONE 0.5 mL/100 mL; CERAMIDE 3 0.2 mL/100 mL; OPUNTIA FICUS-INDICA FRUIT JUICE 0.15 mL/100 mL; SODIUM LAUROYL SARCOSINATE 5 mL/100 mL; DISODIUM COCOYL GLUTAMATE 3 mL/100 mL; DECYL GLUCOSIDE 2 mL/100 mL; SODIUM POLYGLUTAMATE (200000 MW) 1 mL/100 mL; POLYGLYCERYL-10 STEARATE 0.2 mL/100 mL; SODIUM PCA 1 mL/100 mL; 1,2-HEXANEDIOL 1 mL/100 mL; GLYCERIN 5 mL/100 mL; BUTYLENE GLYCOL 5 mL/100 mL; PROPYLENE GLYCOL 0.2 mL/100 mL; KOJIC ACID 1 mL/100 mL; TREHALOSE 0.2 mL/100 mL; SOPHORA FLAVESCENS ROOT 0.15 mL/100 mL; SODIUM CHLORIDE 0.5 mL/100 mL; SUCROSE STEARATE 0.2 mL/100 mL

ALARMS

For external use only. Extremely Flammable: Avoid fire, flame, or smoking during andimmediately following application.

KEEP OUT OF REACH OF CHILDREN

swallowed, get medical help or contact a Poison Control Center rightaway.(+1 818 579 7288)right away.

INACTIVE INGREDIENT

AQUA-GLYCERIN-BUTYLENE GLYCOL-SODIUM LAUROYL SARCOSINATE-DISODIUM COCOYL GLUTAMATE-DECYL GLUCOSIDE-SODIUM LAUROYL GLUTAMATE-KOJIC ACID-SODIUM PCA-1,2-HEXANEDIOL-CHRYSANTHELLUM INDICUM EXTRACT-SODIUM POLYGLUTAMATE-OLEA EUROPAEA (OLIVE) FRUIT OIL-SODIUM CHLORIDE-HYDROXYACETOPHENONE-PROPYLENE GLYCOL-CERAMIDE 3-POLYGLYCERYL-10 STEARATE-TREHALOSE-BAKUMONDOU EKISU-OPUNTIA FICUS-INDICA FRUIT EXTRACT-SOPHORA FLAVESCENS ROOT EXTRACT-CITRIC ACID-HYDROGENATED LECITHIN-SUCROSE STEARATE

STORAGE AND HANDLING

Before use, read all information on carton and enclosed leaflet

Store at controlled room temperature 20° to 25℃ (68° to 77°F).Do not incinerate container, Do not expose to heat or store attemperature abowe 120°F (49°C).

DOSAGE AND ADMINISTRATION

Pump an adequate amount of the mousse into your hands. The rich foam will form instantly
Gently massage the foam onto damp skin in circular motions, focusing on areas prone to dirt and oil, like the forehead, nose, and chin
Rinse thoroughly with lukewarm water and pat dry with a clean towel

For best results, use twice daily—morning and evening. Follow with your favorite toner, serum, and moisturizer for a complete skincare routine.

WHEN USING

For external use only. Please keep out of children. Do not swallow. Please clean your hands before use to ensure the best results from the product. Discontinue use if signs of irritation or rash occur. Store the product in a cool, dry place, away from direct sunlight and heat.

STOP USE

Discontinue use if signs of rash occur. Discontinue use if irritation occurs. Discontinue use if allergic to any of the ingredients listed.

Do not use on injured skin. Do not use if allergic to any of the ingredients listed. If you use other medications on your skin, consult your doctor before using them. Do not use if your skin appears red, irritated, or allergic.

ACTIVE INGREDIENT

TURMERIC & KOJIC ACID

WARNINGS

For external use only. Please keep out of children. Do not swallow.

INDICATIONS AND USAGE

For cleansing facial skin

PURPOSE

facial cleansing